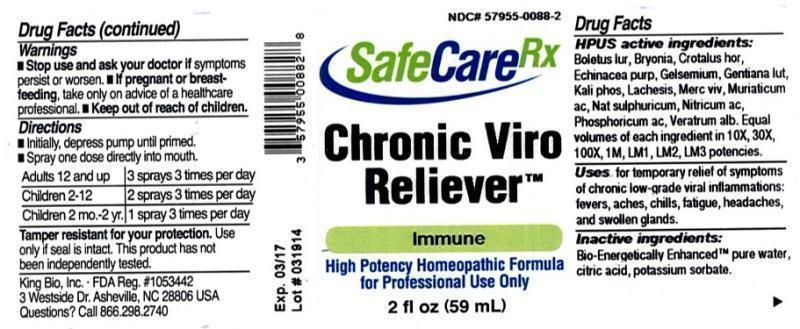 DRUG LABEL: Chronic Viro Reliever
NDC: 57955-0088 | Form: LIQUID
Manufacturer: King Bio Inc.
Category: homeopathic | Type: HUMAN OTC DRUG LABEL
Date: 20140331

ACTIVE INGREDIENTS: BOLETUS LURIDUS FRUITING BODY 10 [hp_X]/59 mL; BRYONIA ALBA ROOT 10 [hp_X]/59 mL; CROTALUS HORRIDUS HORRIDUS VENOM 10 [hp_X]/59 mL; ECHINACEA PURPUREA 10 [hp_X]/59 mL; GELSEMIUM SEMPERVIRENS ROOT 10 [hp_X]/59 mL; GENTIANA LUTEA ROOT 10 [hp_X]/59 mL; POTASSIUM PHOSPHATE, DIBASIC 10 [hp_X]/59 mL; LACHESIS MUTA VENOM 10 [hp_X]/59 mL; MERCURY 10 [hp_X]/59 mL; HYDROCHLORIC ACID 10 [hp_X]/59 mL; SODIUM SULFATE 10 [hp_X]/59 mL; NITRIC ACID 10 [hp_X]/59 mL; PHOSPHORIC ACID 10 [hp_X]/59 mL; VERATRUM ALBUM ROOT 10 [hp_X]/59 mL
INACTIVE INGREDIENTS: WATER; CITRIC ACID MONOHYDRATE; POTASSIUM SORBATE

Chronic Viro Reliever

ACTIVE INGREDIENT

HPUS active ingredients: Boletus luridus, Bryonia, Crotalus horridus, Echinacea purpurea, Gelsemium sempervirens, Gentiana lutea, Kali phosphoricum, Lachesis mutus, Mercurius vivus, Muriaticum acidum, Natrum sulphuricum, Nitricum acidum, Phosphoricum acidum, Veratrum album . Equal volumes of each ingredient in 10X, 30X, 100X, 1M, LM1, LM2, LM3 potencies.

PURPOSE

Uses for temporary relief of symptoms of chronic low-grade viral inflammations: fevers, aches, chills, fatigue, headaches, and swollen glands.

Inactive Ingredients

Bio-Energetically Enhanced™ pure water base, Citric acid and Potassium sorbate.

Warning

- Stop use and ask your doctor if symptoms persist or worsen.
- If pregnant or breast-feeding, take only on advice of a healthcare professional.

- Keep out of reach of children.

Directions

- Initially, depress pump until primed.
- Spray one dose directly into mouth.
- Adults 12 and up: 3 sprays 3 times per day.
- Children 2-12: 2 sprays 3 times per day.
- Children 2 mo.-2 yr: 1 spray 3 times per day

Other Information

- Tamper resistant for your protection.
- Use only if seal is intact.
- This product has not been independently tested.

INDICATIONS AND USAGE

Uses for temporary relief of symptoms of chronic low-grade viral inflammations:

- fevers
- aches
- chills
- fatigue
- headaches
- swollen glands